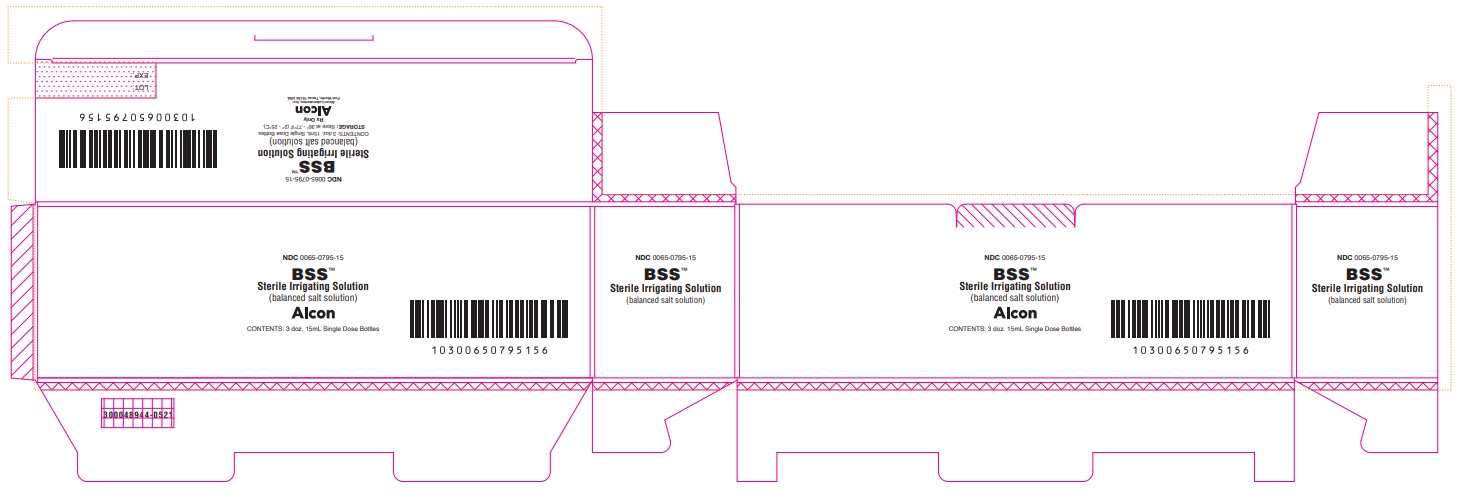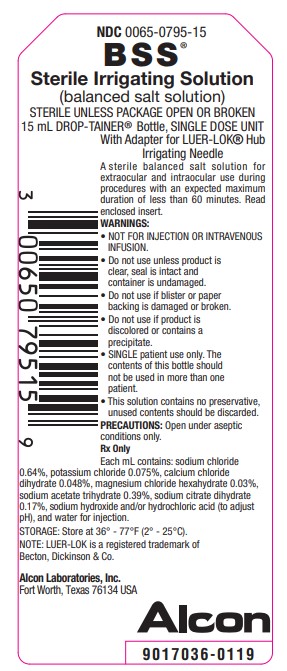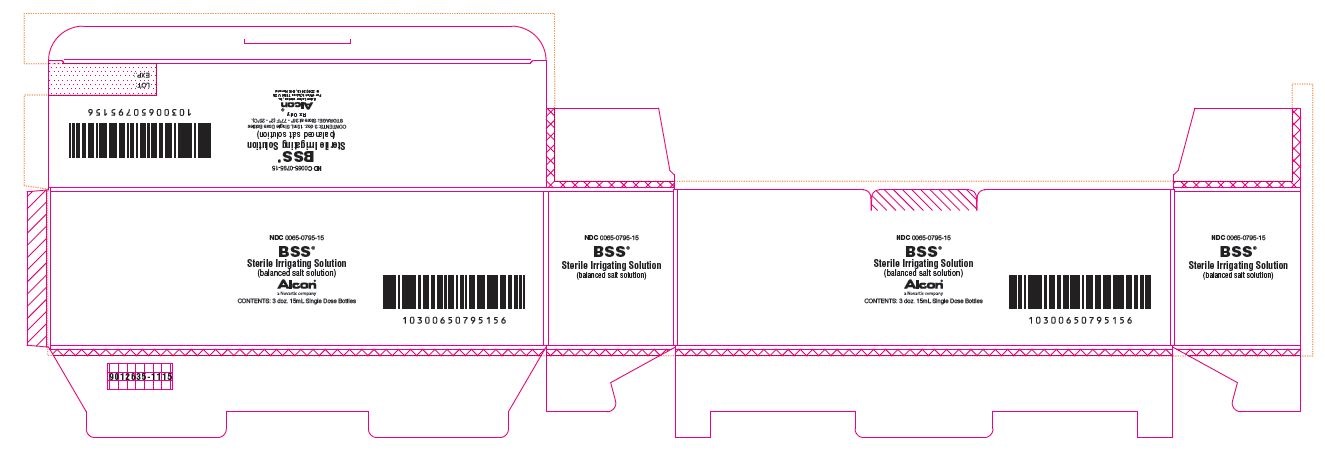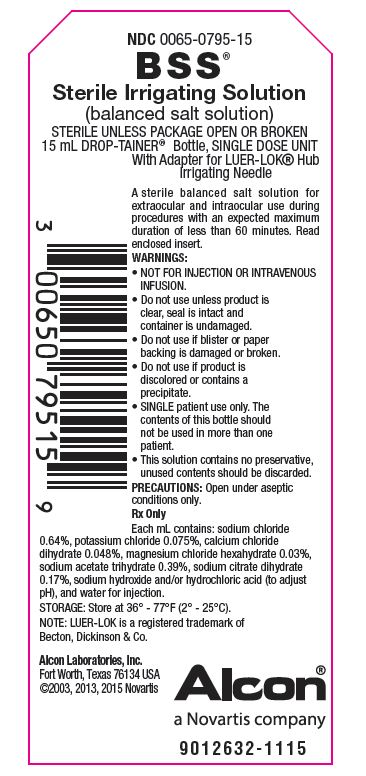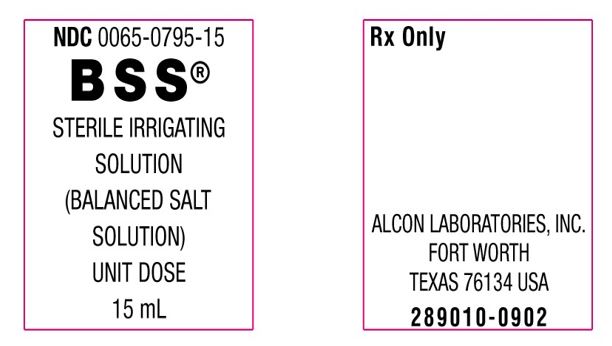 DRUG LABEL: BSS
NDC: 0065-0795 | Form: SOLUTION
Manufacturer: Alcon Laboratories, Inc.
Category: prescription | Type: HUMAN PRESCRIPTION DRUG LABEL
Date: 20240125

ACTIVE INGREDIENTS: SODIUM CHLORIDE 6.4 mg/1 mL; POTASSIUM CHLORIDE 0.75 mg/1 mL; CALCIUM CHLORIDE 0.48 mg/1 mL; MAGNESIUM CHLORIDE 0.3 mg/1 mL; SODIUM ACETATE 3.9 mg/1 mL; SODIUM CITRATE 1.7 mg/1 mL
INACTIVE INGREDIENTS: SODIUM HYDROXIDE; HYDROCHLORIC ACID; WATER

BSS™
Sterile Irrigating Solution
(balanced salt solution)

DESCRIPTION

BSS™ Sterile Irrigating Solution is a sterile balanced salt solution, each mL containing sodium chloride (NaCl) 0.64%, potassium chloride (KCl) 0.075%, calcium chloride dihydrate (CaCl2•2H2O) 0.048%, magnesium chloride hexahydrate (MgCl2•6H2O) 0.03%, sodium acetate trihydrate (C2H3NaO2•3H2O) 0.39%, sodium citrate dihydrate (C6H5Na3O7•2H2O) 0.17%, sodium hydroxide and/or hydrochloric acid (to adjust pH), and water for injection. The pH is approximately 7.5. The osmolality is approximately 300 mOsm/Kg.

CLINICAL PHARMACOLOGY

BSS Sterile Irrigating Solution is an isotonic solution for use in irrigating tissues of the eyes.

INDICATIONS AND USAGE

For use as an extraocular and intraocular irrigating solution during ocular surgical procedure involving perfusion of the eye with an expected maximum duration of less than 60 minutes.

WARNINGS

• NOT FOR INJECTION OR INTRAVENOUS INFUSION.

• Do not use unless product is clear, seal is intact, and container is undamaged.

• Do not use if product is discolored or contains a precipitate.

• SINGLE patient use only. The contents of this bottle should not be used in more than one patient.

• This solution contains no preservative, unused contents should be discarded.

PRECAUTIONS

Open under aseptic conditions only.

Prior to use, check the following: tip should be firmly in place, irrigating needle should be properly seated; squeeze out several drops before inserting into anterior chamber. The needle should be removed from the anterior chamber prior to releasing pressure to prevent suction.

Studies suggest that intraocular irrigating solutions which are iso-osmotic with normal aqueous fluids should be used with caution in diabetic patients undergoing vitrectomy since intraoperative lens changes have been observed.

There have been reports of corneal clouding or edema following ocular surgery in which BSS Sterile Irrigating Solution was used as an irrigating solution.

ADVERSE REACTIONS

Irrigation or any other trauma to the corneal endothelium may result in corneal swelling or bullous keratopathy. Post-operative inflammatory reactions as well as incidents of corneal edema and corneal decompensation have been reported.

DOSAGE AND ADMINISTRATION

The adapter plug is designed to accept an irrigating needle. Tissues may be irrigated by attaching the needle to the DROP-TAINER® bottle as explained below. External irrigation may be done without the irrigating needle.

Method of using Adapter Plug for LUER-LOK® Hub Ophthalmic Irrigating Needle:

1. Aseptically remove DROP-TAINER bottle from blister by peeling paper backing.

2. Snap on surgeon's sterile irrigation needle. Push until firmly in place and twist slightly.

3. Test assembly for proper function before use.

NOTE: LUER-LOK is a registered trademark of Becton, Dickinson and Company.

HOW SUPPLIED

In 15 mL and 30 mL sterile DROP-TAINER bottles (consisting of a polypropylene bottle and LEUR-LOK™ adapter plug with a white polypropylene closure) in a blister package.

15 mL in a 15 mL bottle:
NDC0065-0795-15

30 mL in a 30 mL bottle:
NDC0065-0795-30

STORAGE:Store at 36° - 77°F (2° - 25°C).

Revised: May 2021

Alcon

Distributed by:
Alcon Laboratories , Inc.
6201 South Freeway
Fort Worth, Texas 76134 USA

© 2021 Alcon Inc.
W300048945-0521

PRINCIPAL DISPLAY PANEL

NDC 0065-0795-15
BSS™
Sterile Irrigating Solution
(balanced salt solution)
ALCON
CONTENTS: 3 doz. 15mL Single Dose Bottles
STORAGE: Store at 36° - 77°F (2° - 25°C).
Rx Only
Alcon
Alcon Laboratories, Inc.
Fort Worth, Texas 76134 USA
300048944-0521

NDC 0065-0795-15
BSS®
Sterile Irrigating Solution
(balanced salt solution)
ALCON®
a Novartis company
CONTENTS: 3 doz. 15mL Single Dose Bottles
STORAGE: Store at 36° - 77°F (2° - 25°C).
Rx Only
Alcon®
Alcon Laboratories, Inc.
Fort Worth, Texas 76134 USA
© 2002, 2013, 2015 Novartis
9012635-1115

NDC 0065-0795-15
BSS®
Sterile Irrigating Solution
(balanced salt solution)
STERILE UNLESS PACKAGE OPEN OR BROKEN
15 mL DROP-TAINER® Bottle, SINGLE DOSE UNIT With Adapter for LUER-LOK® Hub Irrigating Needle
A sterile balanced salt solution for
extraocular and intraocular use during
procedures with an expected maximum
duration of less than 60 minutes. Read
enclosed insert.
WARNINGS:
• NOT FOR INJECTION OR INTRAVENOUSINFUSION.
• Do not use unless product is clear, seal is intact and container is undamaged.
• Do not use if blister or paper backing is damaged or broken.
• Do not use if product is discolored or contains a precipitate.
• SINGLE patient use only. The contents of this bottle should not be used in more than one patient.
• This solution contains no preservative, unused contents should be discarded.
PRECAUTIONS: Open under aseptic
conditions only.
Rx Only
Each mL contains: sodium chloride
0.64%, potassium chloride 0.075%, calcium chloride
dihydrate 0.048%, magnesium chloride hexahydrate 0.03%,
sodium acetate trihydrate 0.39%, sodium citrate dihydrate
0.17%, sodium hydroxide and/or hydrochloric acid (to adjust
pH), and water for injection.
STORAGE: Store at 36° - 77°F (2° - 25°C).
NOTE: LUER-LOK is a registered trademark of
Becton, Dickinson & Co.
Alcon Laboratories, Inc.
Fort Worth, Texas 76134 USA
Alcon
9017036-0119

NDC 0065-0795-15
BSS®
Sterile Irrigating Solution
(balanced salt solution)
STERILE UNLESS PACKAGE OPEN OR BROKEN
15 mL DROP-TAINER® Bottle, SINGLE DOSE UNIT With Adapter for LUER-LOK® Hub Irrigating Needle
A sterile balanced salt solution for extraocular and intraocular use during procedures with an expected maximum duration of less than 60 minutes. Read enclosed insert.
WARNINGS:
• NOT FOR INJECTION OR INTRAVENOUS INFUSION.
• Do not use unless product is clear, seal is intact and container is undamaged.
• Do not use if blister or paper backing is damaged or broken.
• Do not use if product is discolored or contains a precipitate.
• SINGLE patient use only. The contents of this bottle should not be used in more than one patient.
• This solution contains no preservative, unused contents should be discarded.
PRECAUTIONS: Open under aseptic conditions only.
Rx Only
Each mL contains: sodium chloride 0.64%, potassium chloride 0.075%, calcium chloride dihydrate 0.048%, magnesium chloride hexahydrate 0.03%, sodium acetate trihydrate 0.39%, sodium citrate dihydrate 0.17%, sodium hydroxide and/or hydrochloric acid (to adjust pH), and water for injection.
STORAGE: Store at 36° - 77°F (2° - 25°C).
NOTE: LUER-LOK is a registered trademark of Becton, Dickinson & Co.
Alcon Laboratories, Inc.
Fort Worth, Texas 76134 USA
©2003, 2013,2015 Novartis
Alcon®
a Novartis company
9012632-1115

NDC 0065-0795-15
BSS®
STERILE IRRIGATING SOLUTION
(BALANCED SALT SOLUTION)
UNIT DOSE 15 mL
Rx Only
ALCON LABORATRIES, INC.
FORT WORTH
TEXAS 76134 USA
289010-0902